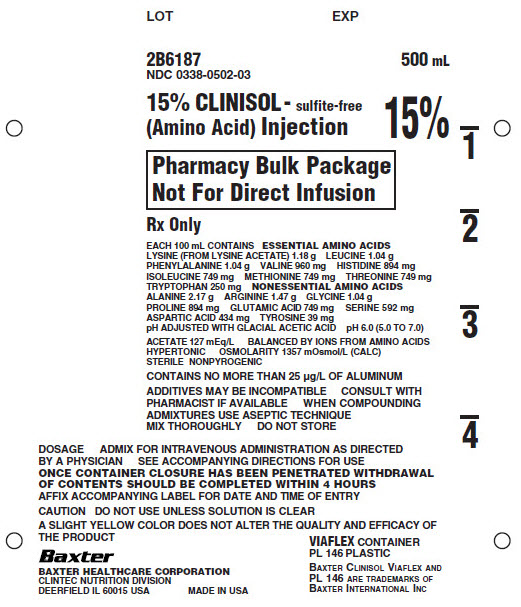 DRUG LABEL: Clinisol
NDC: 0338-0502 | Form: INJECTION, SOLUTION
Manufacturer: Baxter Healthcare Corporation
Category: prescription | Type: HUMAN PRESCRIPTION DRUG LABEL
Date: 20180601

ACTIVE INGREDIENTS: LYSINE ACETATE 1.18 g/100 mL; LEUCINE 1.04 g/100 mL; PHENYLALANINE 1.04 g/100 mL; VALINE 960 mg/100 mL; HISTIDINE 894 mg/100 mL; ISOLEUCINE 749 mg/100 mL; METHIONINE 749 mg/100 mL; THREONINE 749 mg/100 mL; TRYPTOPHAN 250 mg/100 mL; ALANINE 2.17 g/100 mL; ARGININE 1.47 g/100 mL; GLYCINE 1.04 g/100 mL; PROLINE 894 mg/100 mL; GLUTAMIC ACID 749 mg/100 mL; SERINE 592 mg/100 mL; ASPARTIC ACID 434 mg/100 mL; TYROSINE 39 mg/100 mL
INACTIVE INGREDIENTS: ACETIC ACID; WATER

15% CLINISOL - sulfite-free (Amino Acid) Injection
Pharmacy Bulk Package
Not for Direct Infusion
in VIAFLEX Plastic Container

DESCRIPTION

15% CLINISOL - sulfite-free (Amino Acid) Injection Pharmacy Bulk Package is a sterile, clear, nonpyrogenic, hypertonic solution of essential and nonessential amino acids. A Pharmacy Bulk Package is a container of a sterile preparation for parenteral use that contains many single doses. The contents are intended for use in a pharmacy admixture program and are restricted to the preparation of admixtures for intravenous infusion.

The VIAFLEX plastic container is fabricated from a specially formulated polyvinyl chloride (PL 146 Plastic). Exposure to temperatures above 25ºC/77ºF during transport and storage will lead to minor losses in moisture content. Higher temperatures lead to greater losses. It is unlikely that these minor losses will lead to clinically significant changes within the expiration period. The amount of water that can permeate from inside the container into the overwrap is insufficient to affect the solution significantly. Solutions in contact with the plastic container can leach out certain of its chemical components in very small amounts within the expiration period, e.g., di-2-ethylhexyl phthalate (DEHP), up to 5 parts per million; however, the safety of the plastic has been confirmed in tests in animals according to USP biological test for plastic containers as well as by tissue culture toxicity studies.

Each 100 mL of 15% CLINISOL - sulfite-free (Amino Acid) Injection Pharmacy Bulk Package contains:

Amino Acids; Total Nitrogen pH | 15.0 g; 2.37 g; 6.0 (5.0 to 7.0)
(pH adjusted with glacial acetic acid)
Essential Amino Acids; Lysine - (from Lysine Acetate) C6H14N2O2; Leucine - C6H13NO2; Phenylalanine – C9H11NO2; Valine - C5H11NO2; Histidine - C6H9N3O2; Isoleucine - C6H13NO2; Methionine - C5H11NO2S; Threonine - C4H9NO3; Tryptophan - C11H12N2O2; Nonessential Amino Acids; Alanine - C3H7NO2; Arginine - C6H14N4O2; Glycine - C2H5NO2; Proline - C5H9NO2; Glutamic Acid - C5H9NO4; Serine – C3H7NO3; Aspartic Acid – C4H7NO4; Tyrosine – C9H11NO3; Anion profiles per liter*; Acetate from Lysine Acetate and glacial acetic acic; *Balanced by ions from amino acids; Osmolarity (Calc.) | 1.18 g; 1.04 g; 1.04 g; 960 mg; 894 mg; 749 mg; 749 mg; 749 mg; 250 mg; 2.17 g; 1.47 g; 1.04 g; 894 mg; 749 mg; 592 mg; 434 mg; 39 mg; 127 mEq; 1357 mOsmol/L

CLINICAL PHARMACOLOGY

15% CLINISOL - sulfite-free (Amino Acid) Injection Pharmacy Bulk Package administered parenterally will provide biologically utilizable source material for protein synthesis when used with concentrated calorie sources, electrolytes, vitamins and minerals.

Central Infusion

15% CLINISOL - sulfite-free (Amino Acid) Injection Pharmacy Bulk Package is intended for use in a pharmacy admixture program and as such is restricted to the preparation of admixtures for intravenous use. 15% CLINISOL - sulfite-free (Amino Acid) Injection Pharmacy Bulk Package given by central venous infusion in combination with energy sources, vitamins, trace elements and electrolytes, will meet the requirements for weight maintenance or weight gain. The energy component may be derived solely from dextrose or may be provided by a combination of dextrose and intravenous fat emulsion.

Peripheral Infusion

15% CLINISOL - sulfite-free (Amino Acid) Injection Pharmacy Bulk Package, when diluted to an appropriate osmolarity level (718 mOsmol/L) can also be administered by a peripheral vein when use of a central venous catheter is contraindicated.

INDICATIONS AND USAGE

15% CLINISOL - sulfite-free (Amino Acid) Injection Pharmacy Bulk Package is indicated as an adjunct in the offsetting of nitrogen loss or in the treatment of negative nitrogen balance in patients where: (1) the alimentary tract cannot or should not be used, (2) gastrointestinal absorption of protein is impaired, or (3) metabolic requirements for protein are substantially increased, as with extensive burns.

CONTRAINDICATIONS

Hypersensitivity to one or more amino acids

Severe liver disease or hepatic coma

Anuria

Metabolic disorders involving impaired nitrogen utilization

WARNINGS

Additives may be incompatible. Consult with pharmacist, if available. When introducing additives, use aseptic techniques. Mix thoroughly. Do not store. Because of the potential for life-threatening events, caution should be taken to ensure that precipitates have not formed in any parenteral nutrient admixture.

This injection is for compounding only, not for direct infusion.

Once container closure has been penetrated, withdrawal of contents should be completed within 4 hours. After initial entry, maintain contents at room temperature (25ºC/77ºF).

Any admixture storage should be under refrigeration and limited to a brief period of time, preferably less than 24 hours.

Administration of amino acid solutions at excessive rates or to patients with hepatic insufficiency may result in plasma amino acid imbalances, hyperammonemia, prerenal azotemia, stupor and coma. Conservative doses of amino acids should be given to these patients, dictated by the nutritional status of the patient. Should symptoms of hyperammonemia develop, amino acid administration should be discontinued and the patient's clinical status reevaluated.

WARNING: This product contains aluminum that may be toxic. Aluminum may reach toxic levels with prolonged parenteral administration if kidney function is impaired. Premature neonates are particularly at risk because their kidneys are immature, and they require large amounts of calcium and phosphate solutions, which contain aluminum.

Research indicates that patients with impaired kidney function, including premature neonates, who receive parenteral levels of aluminum at greater than 4 to 5 μg/kg/day accumulate aluminum at levels associated with central nervous system and bone toxicity. Tissue loading may occur at even lower rates of administration.

PRECAUTIONS

General

In order for parenterally administered amino acids to be retained by the body and utilized for protein synthesis adequate calories must be administered concurrently.

The administration of 15% CLINISOL - sulfite-free (Amino Acid) Injection Pharmacy Bulk Package as part of total parenteral nutrition (TPN) with large volumes of hyperosmotic fluids requires periodic monitoring of the patient for signs of hyperosmolarity, hyperglycemia, glycosuria and hypertriglyceridemia.

During parenteral nutrition with concentrated dextrose and amino acid solutions, essential fatty acid deficiency syndrome may develop but may not be clinically apparent. Early demonstration of this condition can only be accomplished by analysis of plasma lipids. The syndrome may be prevented or corrected by appropriate treatment with intravenous fat emulsions.

For complete nutritional support, TPN regimens must also include multiple vitamins and trace elements. Potentially incompatible ions such as calcium and phosphate may be added to alternate infusate containers to avoid precipitation.

Initiation and termination of infusions of TPN fluids must be gradual to permit adjustment of endogenous insulin release.

Caution should be exercised against volume overload.

Do not administer unless solution is clear.

TPN delivered through a central or large peripheral vein is a special technique requiring a team effort by physician, nurse and pharmacist. The responsibility for administering this therapy should be confined to those trained in the procedures and alert to signs of complications. Complications known to occur from the placement of central venous catheters include sepsis and vein irritation due to hypertonicity of the infused solution. The risk of sepsis is present during intravenous therapy, especially when using central venous catheters for prolonged periods. It is imperative that the preparation of admixtures and the placement and care of the catheters be accomplished under controlled aseptic conditions. It is essential that a carefully prepared protocol, based on current medical practices be followed.

Drug product contains no more than 25 μg/L of aluminum.

Laboratory Tests

Frequent clinical evaluations and laboratory determinations are necessary for proper monitoring during administration.

Laboratory tests should include blood glucose, serum electrolytes, liver and renal function, serum osmolarity, blood ammonia, serum protein, pH, hematocrit, and WBC. When 15% CLINISOL - sulfite-free (Amino Acid) Injection Pharmacy Bulk Package is combined with electrolytes, care should be used in administering this solution to patients with congestive heart failure, renal failure, edema, adrenal hyperactivity, acid base imbalance and those receiving diuretics or antihypertensive therapy. Serum electrolytes should be monitored daily.

Carcinogenesis, Mutagenesis, Impairment of Fertility:

Long term animal studies with 15% CLINISOL - sulfite-free (Amino Acid) Injection Pharmacy Bulk Package have not been performed to evaluate the carcinogenic potential, mutagenic potential or effects on fertility.

Pregnancy:

Teratogenic Effects

Animal reproduction studies have not been conducted with 15% CLINISOL - sulfite-free (Amino Acid) Injection Pharmacy Bulk Package. It is also not known whether 15% CLINISOL - sulfite-free (Amino Acid) Injection Pharmacy Bulk Package can cause fetal harm when administered to a pregnant woman or can affect reproduction capacity. 15% CLINISOL - sulfite-free (Amino Acid) Injection Pharmacy Bulk Package should be given to a pregnant woman only if clearly needed.

Nursing Mothers:

Caution should be exercised when 15% CLINISOL - sulfite-free (Amino Acid) Injection Pharmacy Bulk Package is administered to a nursing woman.

Pediatric Use:

Safety and effectiveness of 15% CLINISOL - sulfite-free (Amino Acid) Injection in pediatric patients have not been established by adequate and well-controlled studies. However, the use of amino acid injections in pediatric patients as an adjunct in the offsetting of nitrogen loss or in the treatment of negative nitrogen balance is referenced in the medical literature. See Dosage and Administration.

ADVERSE REACTIONS

Local reactions consisting of a warm sensation, erythema, phlebitis and thrombosis at the infusion site have occurred with peripheral intravenous infusion of amino acids. In such cases the infusion site should be changed promptly to another vein. Generalized flushing, fever and nausea also have been reported during peripheral infusions of amino acid solutions.

The following metabolic complications have been reported with administration of TPN: metabolic acidosis and alkalosis, hypophosphatemia, hypocalcemia, osteoporosis, glycosuria, hyperglycemia, hyperosmolar nonketotic states and dehydration, rebound hypoglycemia, osmotic diuresis and dehydration, elevated liver enzymes, hypo- and hypervitaminosis, electrolyte imbalances, hyperammonemia, coma and death.

Sepsis has been reported following intravenous therapy, especially when using central venous catheters for prolonged periods.

Complications known to occur from the placement of central venous catheters are pneumothorax, hemothorax, hydrothorax, artery puncture and transection injury to the brachial plexus, malposition of the catheter, formation of arteriovenous fistula, phlebitis, thrombosis and air and catheter emboli.

DOSAGE AND ADMINISTRATION

Doses which achieve nitrogen equilibrium or positive balance are the most desirable. The dosage on the first day should be approximately half the anticipated optimal dosage and should be increased gradually to minimize glycosuria; similarly, withdrawal should be accomplished gradually to avoid rebound hypoglycemia.

Fat emulsion coadministration should be considered when prolonged (more than 5 days) parenteral nutrition is required in order to prevent essential fatty acid deficiency (EFAD).

Pediatric Use:

Use of 15% CLINISOL - sulfite-free (Amino Acid) Injection in pediatric patients is governed by the same considerations that affect the use of any amino acid solution in pediatrics. The amount administered is dosed on the basis of grams of amino acids/kg of body weight/day. Two to three g/kg of body weight for infants with adequate calories are generally sufficient to satisfy protein needs and promote positive nitrogen balance. Solutions administered by peripheral vein should not exceed twice normal serum osmolarity (718 mOsmol/L).

Parenteral drug products should be inspected visually for particulate matter and discoloration prior to administration.

A slight yellow color does not alter the quality and efficacy of this product.

Additives may be incompatible. Complete information is not available. Those additives known to be incompatible should not be used. Consult with pharmacist, if available. When compounding admixtures, use aseptic technique. Mix thoroughly. Do not store any unused portion of 15% CLINISOL - sulfite-free (Amino Acid) Injection Pharmacy Bulk Package.

Central Vein Infusion

In unstressed adult patients with no unusual nitrogen losses, a minimum dosage of 0.1 gram nitrogen (4.2 mL of 15% CLINISOL - sulfite-free (Amino Acid) Injection Pharmacy Bulk Package) plus 4.4 grams (15 calories) of dextrose/fat emulsion per kilogram of body weight per day is required to achieve nitrogen balance and weight stability. For patients stressed by surgery, trauma or sepsis, and those with unusual nitrogen losses, the dosage required for maintenance may be as high as 0.3 to 0.4 grams of nitrogen (13 to 17 mL 15% CLINISOL - sulfite-free (Amino Acid) Injection Pharmacy Bulk Package) per kilogram of body weight per day, with proportionate increases in non-protein calories. Periodic assessment of nitrogen balance of the individual patient is the best indicator of proper dosage. Use of an infusion pump is advisable to maintain a steady infusion rate during central venous infusion.

Peripheral Infusion

In patients for whom central vein catheterization is not advisable, admixtures with 15% CLINISOL - sulfite-free (Amino Acid) Injection Pharmacy Bulk Package can be administered by peripheral vein. Dilution of 250 mL 15% CLINISOL - sulfite-free (Amino Acid) Injection Pharmacy Bulk Package in 750 mL of 10% dextrose will reduce the osmolarity to a level (718 mOsmol/L) which is more favorable to the maintenance of the integrity of the walls of the veins. If infused simultaneously, fat emulsion will provide a dilution effect upon the osmolarity, as well. In pediatric patients, the final solution should not exceed twice normal serum osmolarity (718 mOsmol/L).

DIRECTIONS FOR USE OF VIAFLEX PLASTIC PHARMACY BULK PACKAGE CONTAINER

Do not use if overpouch has been previously opened or damaged.

To Open

Tear overpouch at notch and remove solution container. Visually inspect the container. If the Admin port protector is damaged, detached, or not present, discard container as solution path sterility may be impaired. Some opacity of the plastic may be observed and will diminish gradually. Check for minute leaks by squeezing inner bag firmly. If leaks are found, discard.

Preparation for Admixing

1. The Pharmacy Bulk Package is to be used only in a suitable aseptic work area.
2. Suspend container.
3. Remove plastic protector from port.
4. Attach a suitable sterile transfer device or dispensing set which allows measured dispensing of the contents. Refer to complete directions accompanying device.

VIAFLEX containers should not be written on directly since ink migration has not been investigated. Affix accompanying label for date and time of entry.

HOW SUPPLIED

15% CLINISOL - sulfite-free (Amino Acid) Injection Pharmacy Bulk Package is available in VIAFLEX plastic containers as follows.

2B6187 | 500 mL | NDC 0338-0502-03
2B6189 | 2000 mL | NDC 0338-0502-06

Exposure of pharmaceutical products to heat should be minimized. Avoid excessive heat. Protect from freezing. It is recommended the product be stored at room temperature (25ºC/77ºF).

Baxter Healthcare Corporation
Deerfield, IL 60015 USA

Printed in USA

Baxter, Clinisol, and Viaflex are trademarks of Baxter International Inc.

07-19-00-0370

Rev. June 2018

PRINCIPAL DISPLAY PANEL

Container Label

LOT

EXP

2B6187
NDC 0338-0502-03

500mL

15% CLINISOL - sulfite-free
(Amino Acid) Injection

15%

Pharmacy Bulk Package
Not For Direct Infusion

Rx Only

EACH 100mL CONTAINS ESSENTIAL AMINO ACIDS
LYSINE (FROM LYSINE ACETATE) 1.18 g LEUCINE 1.04 g
PHENYLALANINE 1.04 g VALINE 960 mg HISTIDINE 894 mg
ISOLEUCINE 749 mg METHIONINE 749 mg THREONINE 749 mg
TRYPTOPHAN 250 mg NONESSENTIAL AMINO ACIDS
ALANINE 2.17 g ARGININE 1.47 g GLYCINE 1.04 g
PROLINE 894 mg GLUTAMIC ACID 749 mg SERINE 592 mg
ASPARTIC ACID 434 mg TYROSINE 39 mg
pH ADJUSTED WITH GLACIAL ACETIC ACID pH 6.0 (5.0 TO 7.0)

ACETATE 127 mEq/L BALANCED BY IONS FROM AMINO ACIDS
HYPERTONIC OSMOLARITY 1357 mOsmol/L (CALC)
STERILE NONPYROGENIC

CONTAINS NO MORE THAN 25µg/L OF ALUMINUM

ADDITIVES MAY BE INCOMPATIBLE CONSULT WITH
PHARMACIST IF AVAILABLE WHEN COMPOUNDING
ADMIXTURES USE ASEPTIC TECHIQUE
MIX THOROUGHLY DO NOT STORE

DOSAGE ADMIX FOR INTRAVEOUS ADMINISTRATION AS DIRECTED
BY A PHYSICIAN SEE ACCOMPANYING DIRECTIONS FOR USE
ONCE CONTAINER CLOSURE HAS BEEN PENETRATED WITHDRAWAL
OF CONTENTS SHOULD BE COMPLETED WITHIN 4 HOURS
AFFIX ACCOMPANYING LABEL FOR DATE AND TIME OF ENTRY

CAUTION DO NOT USE UNLESS SOLUTION IS CLEAR

A SLIGHT YELLOW COLOR DOES NOT ALTER THE QUALITY AND EFFICACY OF
THE PRODUCT

Baxter
BAXTER HEALTHCARE CORPORATION
CLINTEC NUTRITION DIVISION
DEERFIELD IL 60015 USA
MADE IN THE USA

VIAFLEX CONTAINER
PL 146 PLASTIC

BAXTER CLINISOL VIAFLEX AND
PL 146 ARE TRADEMARKS OF
BAXTER INTERNATIONAL INC

1

2

3

4